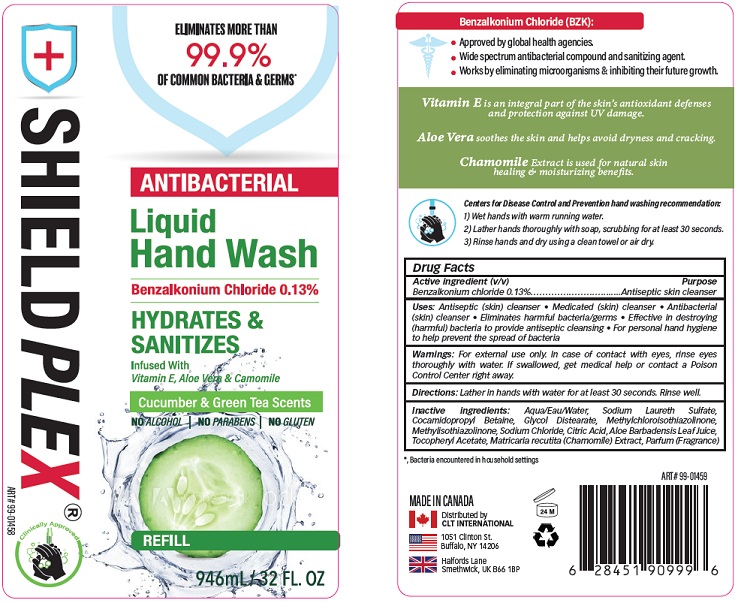 DRUG LABEL: Shieldplex antibacterial hand wash
NDC: 75490-004 | Form: SOAP
Manufacturer: CLT Logistics Inc.
Category: otc | Type: HUMAN OTC DRUG LABEL
Date: 20220209

ACTIVE INGREDIENTS: BENZALKONIUM CHLORIDE 0.13 g/100 mL
INACTIVE INGREDIENTS: WATER; SODIUM LAURETH SULFATE; COCAMIDOPROPYL BETAINE; GLYCOL DISTEARATE; METHYLCHLOROISOTHIAZOLINONE; METHYLISOTHIAZOLINONE; SODIUM CHLORIDE; CITRIC ACID MONOHYDRATE; ALOE VERA LEAF; .ALPHA.-TOCOPHEROL ACETATE; CHAMOMILE

Active Ingredient

Benzalkonium chloride 0.13%

Purpose

Antiseptic skin cleanser

Uses

- Antiseptic (skin) cleanser.
- Medicated (skin) cleanser.
- Antibacterial (skin) cleanser.
- Eliminates harmful bacteria/germs.
- Effective in destroying (harmful) bacteria to provide antiseptic cleansing.
- For personal hand hygiene to help prevent the spread of bacteria.

Warnings

For external use only. In case of contact with eyes, rinse eyes thoroughly with water.

KEEP OUT OF REACH OF CHILDREN

If swallowed, get medical help or contact a Poison Control Center right away.

Directions

Lather in hands with water for at least 30 seconds. Rinse well.

Inactive ingredients

Aqua/Eau/Water, Sodium Laureth Sulfate, Cocamidopropyl Betaine, Glycol Distearate, Methylchloroisothiazolinone, Methylisothiazolinone, Sodium Chloride, Citric Acid, Aloe Barbadensis Leaf Juice, Tocopheryl Acetate, Matricaria recutita (Chamomile) Extract, Parfum (Fragrance).